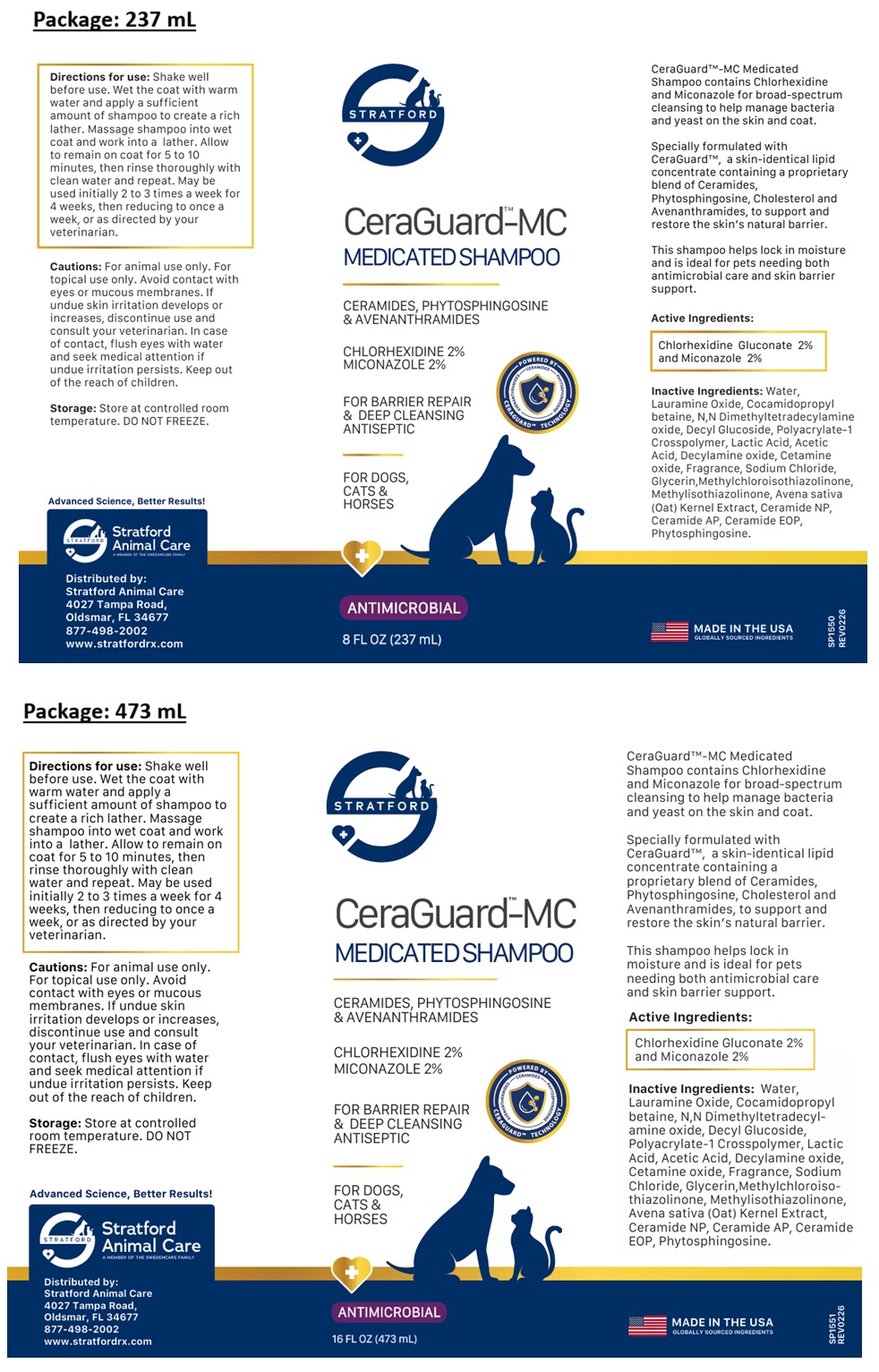 DRUG LABEL: STRATFORD CeraGuard-MC MEDICATED
NDC: 86069-140 | Form: SHAMPOO
Manufacturer: Stratford Care Usa, Inc.
Category: animal | Type: OTC ANIMAL DRUG LABEL
Date: 20260204

ACTIVE INGREDIENTS: CHLORHEXIDINE GLUCONATE 2 g/100 mL; MICONAZOLE 2 g/100 mL
INACTIVE INGREDIENTS: WATER; LAURAMINE OXIDE; COCAMIDOPROPYL BETAINE; MYRISTAMINE OXIDE; DECYL GLUCOSIDE; POLYACRYLATE-1 CROSSPOLYMER; LACTIC ACID, UNSPECIFIED FORM; ACETIC ACID; DECYLAMINE OXIDE; PALMITAMINE OXIDE; SODIUM CHLORIDE; GLYCERIN; METHYLCHLOROISOTHIAZOLINONE; METHYLISOTHIAZOLINONE; OAT; CERAMIDE NP; CERAMIDE AP; CERAMIDE 9; PHYTOSPHINGOSINE

STRATFORD CeraGuardTM-MC MEDICATED SHAMPOO

CeraGuard™-MC Medicated Shampoo contains Chlorhexidine and Miconazole for broad-spectrum cleansing to help manage bacteria and yeast on the skin and coat.

Specially formulated with CeraGuard™, a skin-identical lipid concentrate containing a proprietary blend of Ceramides, Phytosphingosine, Cholesterol and Avenanthramides, to support and restore the skin’s natural barrier.

This shampoo helps lock in moisture and is ideal for pets needing both antimicrobial care and skin barrier support.

Active Ingredients:

Chlorhexidine Gluconate 2% and Miconazole 2%

Inactive Ingredients:

Water, Lauramine Oxide, Cocamidopropyl betaine, N,N Dimethyltetradecylamine oxide, Decyl Glucoside, Polyacrylate-1 Crosspolymer, Lactic Acid, Acetic Acid, Decylamine oxide, Cetamine oxide, Fragrance, Sodium Chloride, Glycerin, Methylchloroisothiazolinone, Methylisothiazolinone, Avena sativa (Oat) Kernel Extract, Ceramide NP, Ceramide AP, Ceramide EOP, Phytosphingosine.

Directions for use:

Shake well before use. Wet the coat with warm water and apply a sufficient amount of shampoo to create a rich lather. Massage shampoo into wet coat and work into a lather. Allow to remain on coat for 5 to 10 minutes, then rinse thoroughly with clean water and repeat. May be used initially 2 to 3 times a week for 4 weeks, then reducing to once a week, or as directed by your veterinarian.

Cautions:

For animal use only. For topical use only. Avoid contact with eyes or mucous membranes. If undue skin irritation develops or increases, discontinue use and consult your veterinarian. In case of contact, flush eyes with water and seek medical attention if undue irritation persists. Keep out of the reach of children.

Storage:

Store at controlled room temperature. DO NOT FREEZE.

CERAMIDES, PHYTOSPHINGOSINE & AVENANTHRAMIDES

FOR BARRIER REPAIR & DEEP CLEANSING ANTISEPTIC

FOR DOGS, CATS & HORSES

ANTIMICROBIAL

MADE IN THE USA
GLOBALLY SOURCED INGREDIENTS

Advanced Science, Better Results!

Stratford Animal Care
A MEMBER OF THE SWEDENCARE FAMILY

Distributed by:
Stratford Animal Care
4027 Tampa Road,
Oldsmar, FL 34677
877-498-2002
www.stratfordrx.com